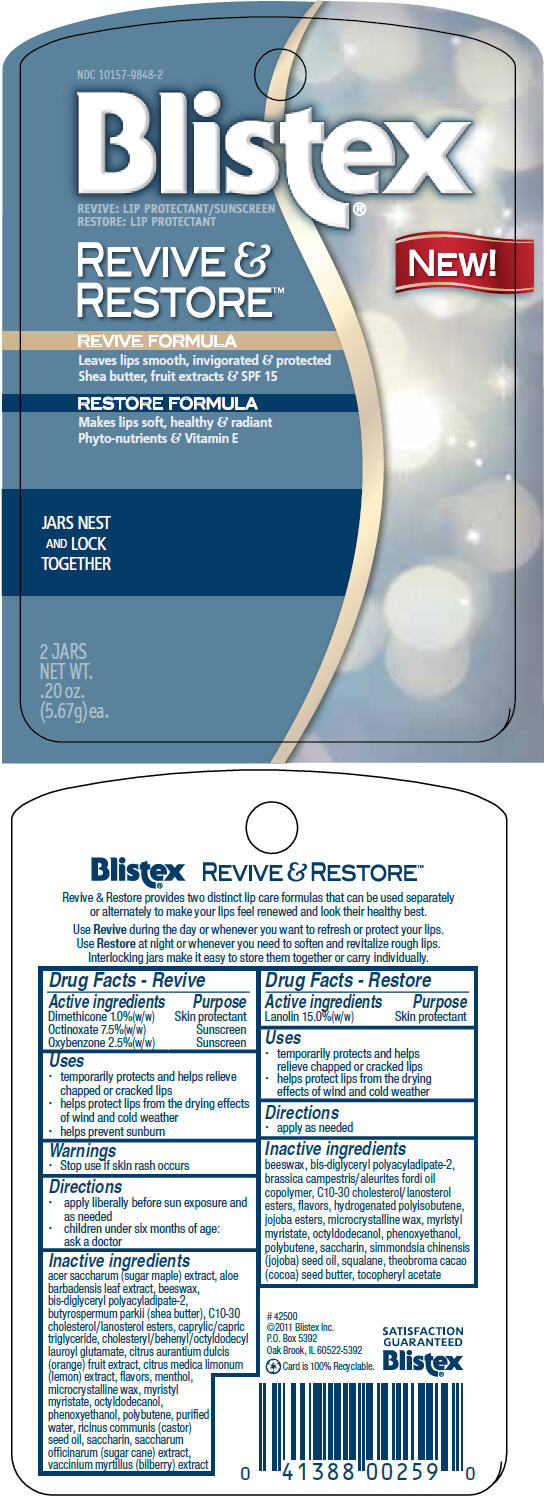 DRUG LABEL: Blistex 
NDC: 10157-9848 | Form: KIT | Route: TOPICAL
Manufacturer: Blistex Inc.
Category: otc | Type: HUMAN OTC DRUG LABEL
Date: 20110824

ACTIVE INGREDIENTS: DIMETHICONE 1 g/100 g; OCTINOXATE 7.5 g/100 g; OXYBENZONE 2.5 g/100 g; LANOLIN 15 g/100 g
INACTIVE INGREDIENTS: ACER SACCHARUM BARK/SAP; ALOE VERA LEAF; YELLOW WAX; SHEA BUTTER; C10-30 CHOLESTEROL/LANOSTEROL ESTERS; MEDIUM-CHAIN TRIGLYCERIDES; ORANGE; LEMON; MENTHOL; MICROCRYSTALLINE WAX; MYRISTYL MYRISTATE; OCTYLDODECANOL; PHENOXYETHANOL; WATER; CASTOR OIL; SACCHARIN; SUGARCANE; BILBERRY; YELLOW WAX; C10-30 CHOLESTEROL/LANOSTEROL ESTERS; MICROCRYSTALLINE WAX; MYRISTYL MYRISTATE; OCTYLDODECANOL; PHENOXYETHANOL; SACCHARIN; JOJOBA OIL; SQUALANE; COCOA BUTTER

Blistex®
REVIVE &
RESTORE™

Drug Facts - Revive

ACTIVE INGREDIENT

Active ingredients | Purpose
Dimethicone 1.0%(w/w) | Skin protectant
Octinoxate 7.5%(w/w) | Sunscreen
Oxybenzone 2.5%(w/w) | Sunscreen

Uses

- temporarily protects and helps relieve chapped or cracked lips
- helps protect lips from the drying effects of wind and cold weather
- helps prevent sunburn

Warnings

- Stop use if skin rash occurs

Directions

- apply liberally before sun exposure and as needed
- children under six months of age:
  ask a doctor

Inactive ingredients

acer saccharum (sugar maple) extract, aloe barbadensis leaf extract, beeswax, bis-diglyceryl polyacyladipate-2, butyrospermum parkii (shea butter), C10-30 cholesterol/lanosterol esters, caprylic/capric triglyceride, cholesteryl/behenyl/octyldodecyl lauroyl glutamate, citrus aurantium dulcis (orange) fruit extract, citrus medica limonum (lemon) extract, flavors, menthol, microcrystalline wax, myristyl myristate, octyldodecanol, phenoxyethanol, polybutene, purified water, ricinus communis (castor) seed oil, saccharin, saccharum officinarum (sugar cane) extract, vaccinium myrtillus (bilberry) extract

Drug Facts - Restore

Active ingredients

Lanolin 15.0%(w/w)

Purpose

Skin protectant

Uses

- temporarily protects and helps relieve chapped or cracked lips
- helps protect lips from the drying effects of wind and cold weather

Directions

- apply as needed

Inactive ingredients

beeswax, bis-diglyceryl polyacyladipate-2, brassica campestris/aleurites fordi oil copolymer, C10-30 cholesterol/lanosterol esters, flavors, hydrogenated polyisobutene, jojoba esters, microcrystalline wax, myristyl myristate, octyldodecanol, phenoxyethanol, polybutene, saccharin, simmondsia chinensis (jojoba) seed oil, squalane, theobroma cacao (cocoa) seed butter, tocopheryl acetate

PRINCIPAL DISPLAY PANEL - Kit Package

NDC 10157-9848-2

Blistex®
REVIVE: LIP PROTECTANT/SUNSCREEN
RESTORE: LIP PROTECTANT

REVIVE &
RESTORE™

REVIVE FORMULA
Leaves lips smooth, invigorated & protected
Shea butter, fruit extracts & SPF 15

RESTORE FORMULA
Makes lips soft, healthy & radiant
Phyto-nutrients & Vitamin E

JARS NEST
AND LOCK
TOGETHER

2 JARS
NET WT.
.20 oz.
(5.67g)ea.

NEW!